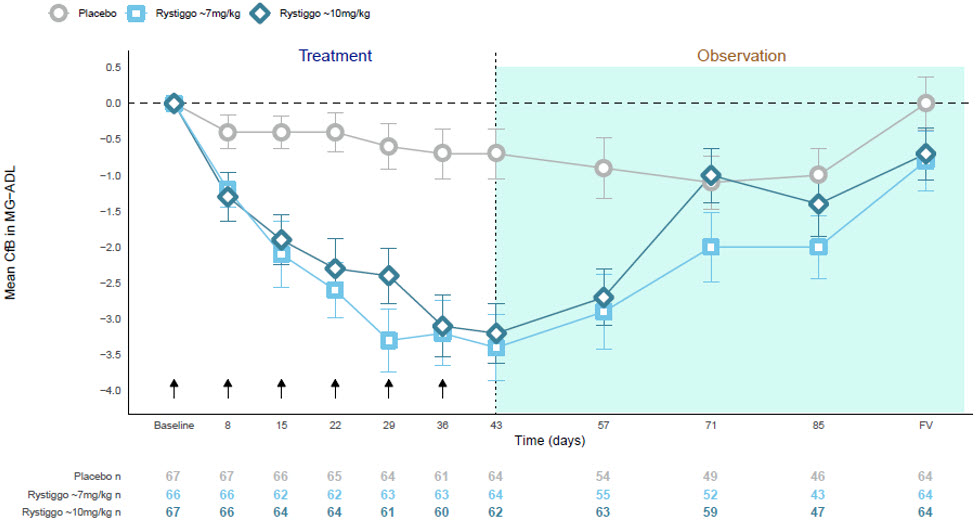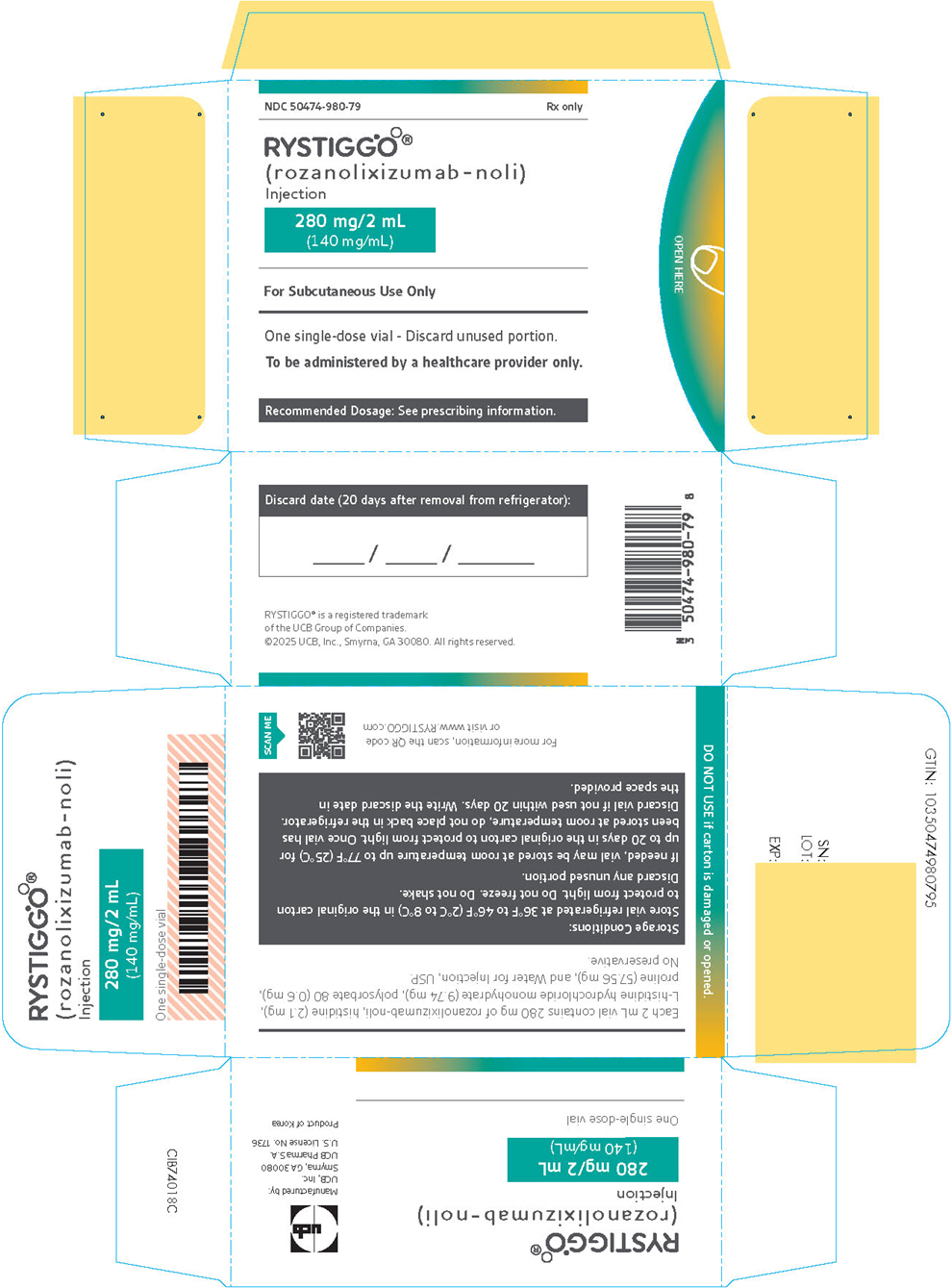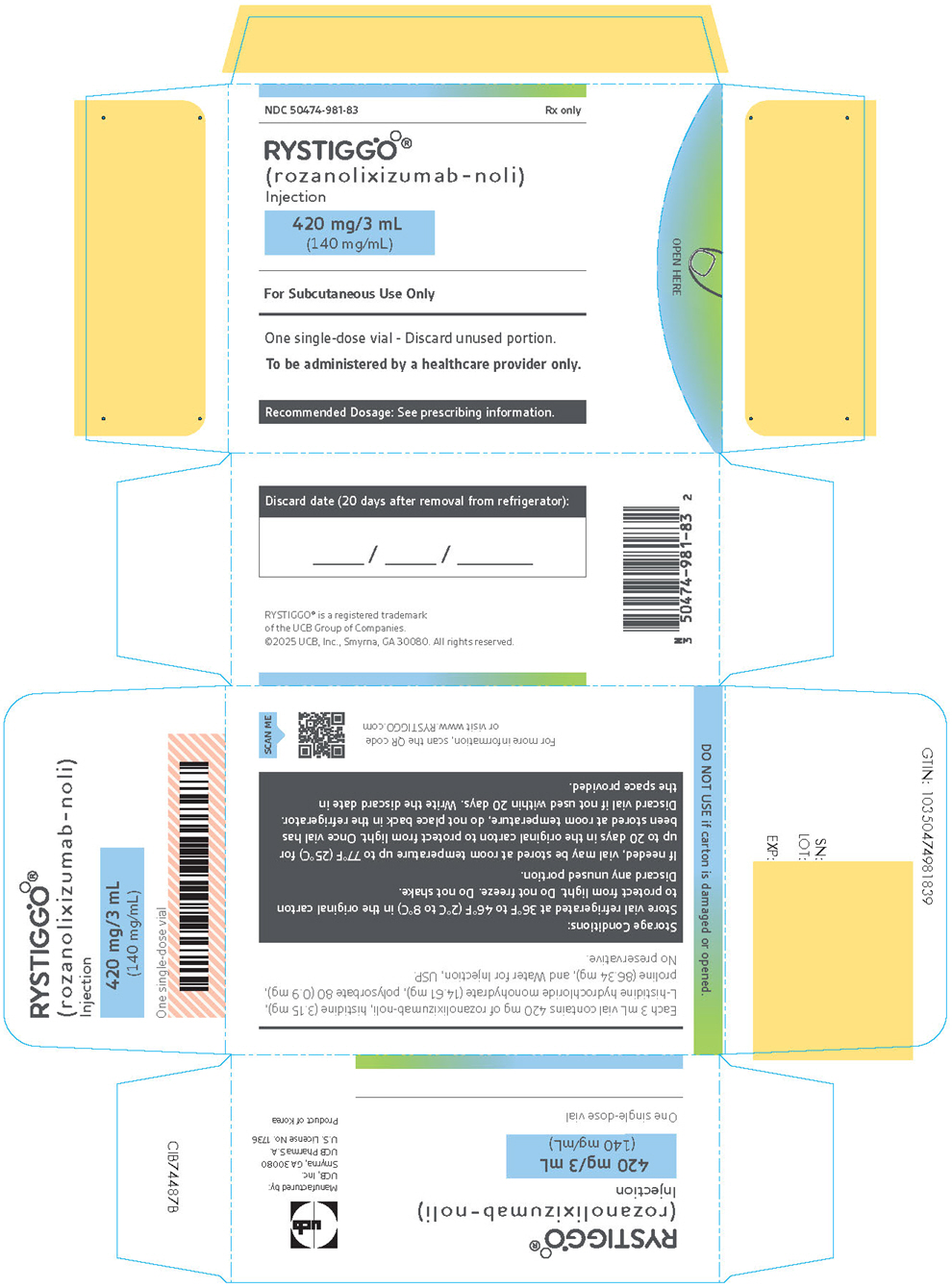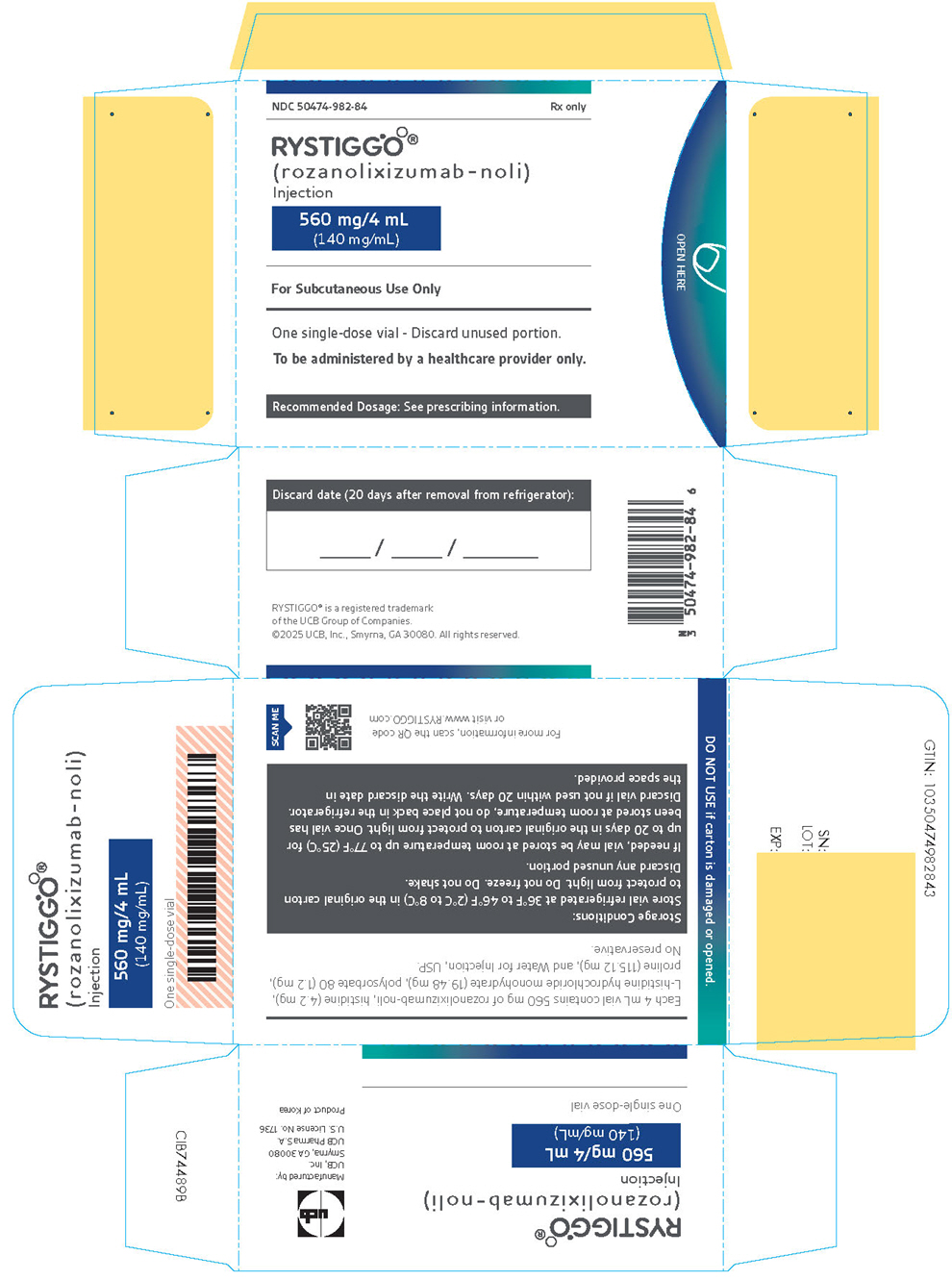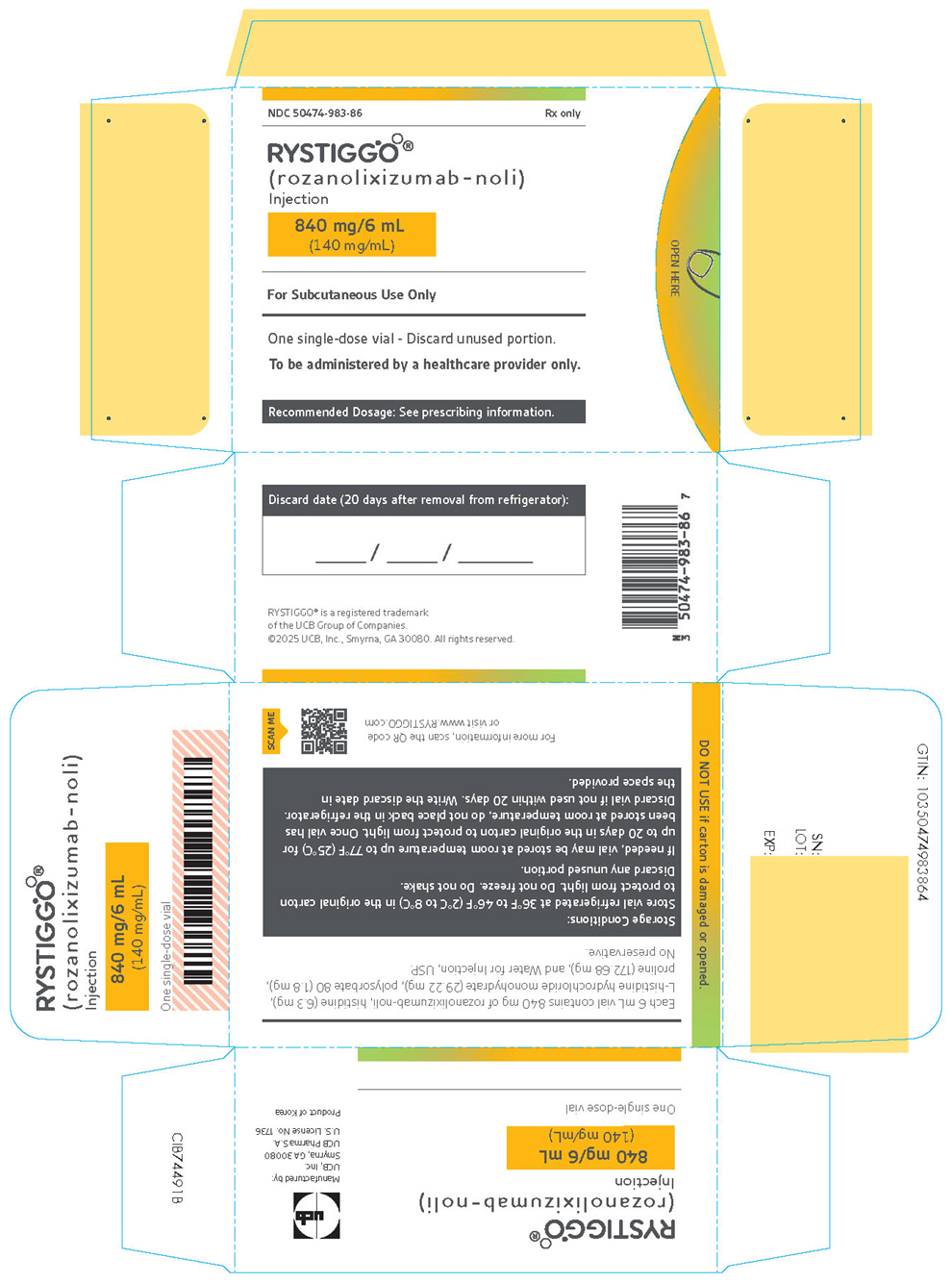 DRUG LABEL: RYSTIGGO
NDC: 50474-980 | Form: INJECTION, SOLUTION
Manufacturer: UCB, Inc.
Category: prescription | Type: HUMAN PRESCRIPTION DRUG LABEL
Date: 20260120

ACTIVE INGREDIENTS: ROZANOLIXIZUMAB 140 mg/1 mL

HIGHLIGHTS OF PRESCRIBING INFORMATION

These highlights do not include all the information needed to use RYSTIGGO safely and effectively. See full prescribing information for RYSTIGGO.
RYSTIGGO®(rozanolixizumab-noli) injection, for subcutaneous use
Initial U.S. Approval: 2023

RECENT MAJOR CHANGES

Dosage and Administration (2.3) | 8/2025

1 INDICATIONS AND USAGE

RYSTIGGO (rozanolixizumab-noli) is a neonatal Fc receptor blocker indicated for the treatment of generalized myasthenia gravis (gMG) in adult patients who are anti-acetylcholine receptor (AChR) or anti-muscle-specific tyrosine kinase (MuSK) antibody positive. (1)

2 DOSAGE AND ADMINISTRATION

- Evaluate the need to administer age-appropriate vaccines according to immunization guidelines before initiation of a new treatment cycle with RYSTIGGO. (2.1)
- For subcutaneous infusion only. (2.2)
- The recommended dosage is administered as a subcutaneous infusion once weekly for 6 weeks. (2.2)
  Body Weight of Patient | Dose | Volume to be Infused
  Less than 50 kg | 420 mg | 3 mL
  50 kg to less than 100 kg | 560 mg | 4 mL
  100 kg and above | 840 mg | 6 mL
- Administer subsequent treatment cycles based on clinical evaluation; the safety of initiating subsequent cycles sooner than 63 days from the start of the previous treatment cycle has not been established. (2.2)

3 DOSAGE FORMS AND STRENGTHS

Injection:

- 280 mg/2 mL (140 mg/mL) in a single-dose vial. (3)
- 420 mg/3 mL (140 mg/mL) in a single-dose vial. (3)
- 560 mg/4 mL (140 mg/mL) in a single-dose vial. (3)
- 840 mg/6 mL (140 mg/mL) in a single-dose vial. (3)

4 CONTRAINDICATIONS

None. (4)

5 WARNINGS AND PRECAUTIONS

- Infections: Delay administration of RYSTIGGO to patients with an active infection. Monitor for signs and symptoms of infection in patients treated with RYSTIGGO. If serious infection occurs, administer appropriate treatment and consider withholding RYSTIGGO until the infection has resolved. (5.1)
- Aseptic Meningitis: Serious events of aseptic meningitis have been reported. Monitor for symptoms; diagnostic workup and treatment should be initiated according to the standard of care. (5.2)
- Hypersensitivity Reactions: Angioedema and rash have occurred. If a hypersensitivity reaction occurs, discontinue the infusion and institute appropriate therapy. (5.3)

6 ADVERSE REACTIONS

The most common adverse reactions (≥10%) in patients with gMG are headache, infections, diarrhea, pyrexia, hypersensitivity reactions, and nausea. (6.1)

To report SUSPECTED ADVERSE REACTIONS, contact UCB, Inc. at 1-844-599-2273 or FDA at 1-800-FDA-1088 or www.fda.gov/medwatch.

7 DRUG INTERACTIONS

- Closely monitor for reduced effectiveness of medications that bind to the human neonatal Fc receptor. When concomitant long-term use of such medications is essential for patient care, consider discontinuing RYSTIGGO and using alternate therapies. (7.1)

8 USE IN SPECIFIC POPULATIONS

Pregnancy: Based on animal data, may cause fetal harm. (8.1)

FULL PRESCRIBING INFORMATION

1 INDICATIONS AND USAGE

RYSTIGGO is indicated for the treatment of generalized myasthenia gravis (gMG) in adult patients who are anti-acetylcholine receptor (AChR) or anti-muscle-specific tyrosine kinase (MuSK) antibody positive.

2 DOSAGE AND ADMINISTRATION

2.1 Recommended Vaccination

Because RYSTIGGO causes transient reduction in IgG levels, immunization with live-attenuated or live vaccines is not recommended during treatment with RYSTIGGO. Evaluate the need to administer age-appropriate immunizations according to immunization guidelines before initiation of a new treatment cycle with RYSTIGGO [see Dosage and Administration (2.2)and Warnings and Precautions (5.1)] .

2.2 Recommended Dosage

The recommended dosage of RYSTIGGO is based on body weight, as shown below in Table 1.

Table 1: Recommended Dose Based on Body Weight
Body Weight of Patient | Dose | Volume to be Infused
Less than 50 kg | 420 mg | 3 mL
50 kg to less than 100 kg | 560 mg | 4 mL
100 kg and above | 840 mg | 6 mL

Administer the recommended dosage as a subcutaneous infusion using an infusion pump at a rate of up to 20 mL/hour once weekly for 6 weeks. For detailed preparation and administration instructions, see Preparation and Administration Instructions (2.3).

Administer subsequent treatment cycles based on clinical evaluation. The safety of initiating subsequent cycles sooner than 63 days from the start of the previous treatment cycle has not been established.

If a scheduled dose is missed, RYSTIGGO may be administered up to 4 days after the scheduled time point. Thereafter, resume the original dosing schedule until the treatment cycle is completed.

2.3 Preparation and Administration Instructions

RYSTIGGO should only be prepared and infused by a healthcare provider.

RYSTIGGO is for subcutaneous administration only using an infusion pump. Refer to the infusion pump manufacturer's instructions for full preparation and administration information. It is recommended to use pumps where the administered volume can be pre-set as each vial contains excess volume for priming of the infusion line.

The following criteria are recommended for administration of RYSTIGGO:

- Syringe pump occlusion alarm limits should be at the maximum setting
- Administration tubing length should be 61 cm or shorter
- Infusion set with a needle of 26 gauge or larger should be used.

Read the instructions below before preparing and administering RYSTIGGO solution.

- Use aseptic technique when preparing and administering RYSTIGGO.
- Prior to use, allow vials to reach room temperature for approximately 30 minutes. Do not use heating devices. Keep the vial in the original carton to protect from light until ready to use. Do not shake.
  - Vials may be stored at room temperature up to 77°F (25°C) for a single period of up to 20 days in the original carton [see How Supplied/Storage and Handling (16.2)].
- Infuse RYSTIGGO within 4 hours of puncturing the vial. RYSTIGGO should be administered immediately after priming the infusion set.
- Parenteral drug products should be inspected visually for particulate matter and discoloration prior to administration, whenever solution and container permit. The solution should be colorless to pale brownish-yellow, clear to slightly opalescent. Do not use the vial if the liquid looks cloudy, contains foreign particles, or has changed color.
- Use transfer needles to fill the syringe.
- Remove the needle from the syringe and attach the infusion set to the syringe.
- Follow the device manufacturer's instructions to prepare the pump and prime the tubing.
- Choose an infusion site in the lower right or lower left part of the abdomen below the navel and clean with an alcohol wipe. Do not infuse where the skin is tender, bruised, red, or hard. Avoid infusing into tattoos, scars, or stretch marks. Rotate infusion sites for subsequent administrations.
- Insert the infusion set needle into the infusion site and secure the needle to the skin with sterile gauze and tape or a transparent dressing.
- Infuse RYSTIGGO at a constant flow rate up to 20 mL/hour.
- Monitor patients during administration and for 15 minutes after completion for clinical signs and symptoms of hypersensitivity reactions. If a hypersensitivity reaction occurs during administration, discontinue administration of RYSTIGGO and institute appropriate supportive measures [see Warnings and Precautions (5.3)].
- When the infusion is complete, do not flushthe infusion line as the volume of infusion has been adjusted taking into account the losses in the line.
- Each RYSTIGGO vial is for one-time use only. RYSTIGGO does not contain preservatives. Discard any remaining solution.

3 DOSAGE FORMS AND STRENGTHS

RYSTIGGO is a clear to slightly opalescent, colorless to pale brownish yellow solution available as:

- 280 mg/2 mL (140 mg/mL) in a single-dose vial.
- 420 mg/3 mL (140 mg/mL) in a single-dose vial.
- 560 mg/4 mL (140 mg/mL) in a single-dose vial.
- 840 mg/6 mL (140 mg/mL) in a single-dose vial.

4 CONTRAINDICATIONS

None.

5 WARNINGS AND PRECAUTIONS

5.1 Infections

RYSTIGGO may increase the risk of infection [see Adverse Reactions (6.1)] . Delay RYSTIGGO administration in patients with an active infection until the infection is resolved. During treatment with RYSTIGGO, monitor for clinical signs and symptoms of infection. If serious infection occurs, administer appropriate treatment and consider withholding RYSTIGGO until the infection has resolved.

Immunization

Immunization with vaccines during RYSTIGGO treatment has not been studied. The safety of immunization with live or live-attenuated vaccines and the response to immunization with any vaccine are unknown. Because RYSTIGGO causes a reduction in IgG levels, vaccination with live-attenuated or live vaccines is not recommended during treatment with RYSTIGGO. Evaluate the need to administer age-appropriate vaccines according to immunization guidelines before initiation of a new treatment cycle with RYSTIGGO.

5.2 Aseptic Meningitis

Serious adverse reactions of aseptic meningitis (also called drug-induced aseptic meningitis) have been reported in patients treated with RYSTIGGO [see Adverse Reactions (6.1)] . If symptoms consistent with aseptic meningitis develop, diagnostic workup and treatment should be initiated according to the standard of care.

5.3 Hypersensitivity Reactions

Hypersensitivity reactions, including angioedema and rash, were observed in patients treated with RYSTIGGO [see Adverse Reactions (6.1)] . Management of hypersensitivity reactions depend on the type and severity of the reaction. Monitor patients during treatment with RYSTIGGO and for 15 minutes after the administration is complete for clinical signs and symptoms of hypersensitivity reactions [see Dosage and Administration (2.3)] . If a hypersensitivity reaction occurs, the healthcare professional should institute appropriate measures if needed or the patient should seek medical attention.

6 ADVERSE REACTIONS

The following clinically significant adverse reactions are discussed in greater detail in other sections of the labeling:

- Infections [see Warnings and Precautions (5.1)]
- Aseptic Meningitis [see Warnings and Precautions (5.2)]
- Hypersensitivity Reactions [see Warnings and Precautions (5.3)]

6.1 Clinical Trial Experience

Because clinical trials are conducted under widely varying conditions, adverse reaction rates observed in the clinical trials of a drug cannot be directly compared to rates in the clinical trials of another drug and may not reflect the rates observed in practice.

In clinical studies, the safety of RYSTIGGO has been evaluated in 196 patients who received at least one dose of RYSTIGGO, including 88 patients exposed to at least 5 treatment cycles and 9 patients exposed to at least 10 treatment cycles.

In a placebo-controlled study (Study 1) in patients with gMG, 133 patients received RYSTIGGO [see Clinical Studies (14)] . Of these 133 patients, approximately 56% were female, 68% were White, 12% were Asian, and 6% were of Hispanic or Latino ethnicity. The mean age at study entry was 52.5 years (range 19 to 89 years).

Patients treated with RYSTIGGO received 1 treatment cycle in Study 1. In an extension study, the minimum time for initiating subsequent treatment cycles, specified by study protocol, was 63 days from the start of the previous treatment cycle. Patients treated with RYSTIGGO on average initiated 4 cycles in one year (range 1 to 7 cycles). The median time between start of treatment cycles was 98 days for patients treated with RYSTIGGO who initiated 4 cycles.

Adverse reactions reported in at least 5% of patients treated with RYSTIGGO and more frequently than placebo are summarized in Table 2. The most common adverse reactions (reported in at least 10% of patients treated with RYSTIGGO) were headache, infections, diarrhea, pyrexia, hypersensitivity reactions, and nausea.

Table 2: Adverse Reactions in at least 5% of Patients Treated with RYSTIGGO and More Frequently than in Patients who Received Placebo in Study 1 (Safety Population)
Adverse Reaction | RYSTIGGO (N = 133) % | Placebo (N = 67) %
Headache | 44 | 19
Any infection | 23 | 19
Upper respiratory tract infection | 8 | 6
Diarrhea | 20 | 13
Pyrexia | 17 | 2
Hypersensitivity reactions | 11 | 5
Nausea | 10 | 8
Administration site reactions | 8 | 3
Abdominal pain | 8 | 6
Arthralgia | 7 | 3

Infections

In Study 1 and the extension studies, out of 196 patients treated with RYSTIGGO, 94 (48%) patients reported infections. Common infections (at least 5% frequency) were upper respiratory tract infections (17%), COVID-19 (14%), urinary tract infections (9%), and herpes simplex (6%). Serious infections were reported in 4% of patients treated with RYSTIGGO. Three fatal cases of pneumonia were identified caused by COVID-19 infection in two patients and an unknown pathogen in one patient. Six cases of infections led to discontinuation of RYSTIGGO [see Warnings and Precautions (5.1)].

Aseptic Meningitis

In clinical trials, one patient with gMG and two patients with another neurological disease experienced a serious adverse reaction of drug-induced aseptic meningitis, which led to hospitalization and discontinuation of RYSTIGGO [see Warnings and Precautions (5.2)].

Hypersensitivity Reactions and Administration Site Reactions

In clinical trials, hypersensitivity reactions occurred within 1 day to 2 weeks of administration. One patient discontinued RYSTIGGO due to a hypersensitivity reaction [see Warnings and Precautions (5.3)].

Local reactions at the administration site occurred within 1 to 3 days after the most recent RYSTIGGO infusion.

Headache

In Study 1, seven (5.3%) cases of severe headache were reported in patients treated with RYSTIGGO. None of the patients who received placebo reported severe headache. One patient was hospitalized due to severe headache and one patient discontinued treatment due to severe headache associated with fever, photophobia, phonophobia, nausea, and vertigo.

6.2 Postmarketing Experience

The following adverse reactions have been identified during postapproval use of RYSTIGGO. Because these reactions are reported voluntarily from a population of uncertain size, it is not always possible to reliably estimate their frequency or establish a causal relationship to drug exposure.

Infections: herpes zoster

7 DRUG INTERACTIONS

7.1 Effect of RYSTIGGO on Other Drugs

Concomitant use of RYSTIGGO with medications that bind to the human neonatal Fc receptor (FcRn) (e.g., immunoglobulin products, monoclonal antibodies, or antibody derivatives containing the human Fc domain of the IgG subclass) may lower systemic exposures and reduce effectiveness of such medications. Closely monitor for reduced effectiveness of medications that bind to the human neonatal Fc receptor. When concomitant long-term use of such medications is essential for patient care, consider discontinuing RYSTIGGO and using alternative therapies.

8 USE IN SPECIFIC POPULATIONS

8.1 Pregnancy

Pregnancy Exposure Registry

There is a pregnancy exposure registry that monitors pregnancy outcomes in women exposed to RYSTIGGO during pregnancy. Patients or their healthcare providers may contact UCBCares at 1-844-599-CARE (2273) or email ucbcares@ucb.com, so that information about the exposure of RYSTIGGO during pregnancy and/or breastfeeding can be collected. As a healthcare professional, please ask about becoming a member of the MGBase registry (https://www.mgbase.org).

Risk Summary

There are limited data on RYSTIGGO use in pregnant women to inform a drug-associated risk of major birth defects, miscarriage, or adverse maternal or fetal outcomes. Following administration of rozanolixizumab-noli to pregnant monkeys at doses greater than those used clinically, increases in embryonic death, reduced body weight, and impaired immune function were observed in the absence of maternal toxicity (see Data).

All pregnancies have a background risk of birth defect, loss, or other adverse outcomes. The background rate of major birth defects and miscarriage in the indicated population is unknown. In the U.S. general population, the estimated background risk of major birth defects and miscarriage in clinically recognized pregnancies is 2% to 4% and 15% to 20%, respectively.

Data

Animal Data

Subcutaneous administration of rozanolixizumab-noli (0, 50, or 150 mg/kg) to pregnant monkeys every 3 days throughout pregnancy (gestation day 20 to parturition) resulted in an increase in embryonic death and reduced body weight and impaired immune function in offspring at both doses. A no-effect dose for adverse developmental effects was not identified; the doses tested in monkeys are 10 and 30 times the maximum recommended human dose of approximately 10 mg/kg, on a mg/kg/week basis.

8.2 Lactation

Risk Summary

There are no data on the presence of rozanolixizumab-noli in human milk, the effects on the breastfed infant, or the effects on milk production. Maternal IgG is known to be present in human milk.

The developmental and health benefits of breastfeeding should be considered along with the mother's clinical need for RYSTIGGO and any potential adverse effects on the breastfed child from RYSTIGGO or from the underlying maternal condition.

8.4 Pediatric Use

Safety and effectiveness in pediatric patients have not been established.

8.5 Geriatric Use

Clinical studies of RYSTIGGO did not include sufficient numbers of patients aged 65 and over to determine whether they respond differently from younger adult patients.

11 DESCRIPTION

Rozanolixizumab-noli, a neonatal Fc receptor blocker, is a recombinant, humanized IgG4P monoclonal antibody, expressed in a genetically engineered Chinese hamster ovary DG44 cell line. Rozanolixizumab-noli has an approximate molecular weight of 148 kDa.

RYSTIGGO 140 mg/mL (2 mL, 3 mL, 4 mL, and 6 mL vials)

RYSTIGGO (rozanolixizumab-noli) injection is a sterile, preservative-free, clear to slightly opalescent, colorless to pale brownish yellow solution for subcutaneous infusion. Each single-dose vial contains 280 mg, 420 mg, 560 mg, or 840 mg of rozanolixizumab-noli at a concentration of 140 mg/mL with a pH of 5.6. Each mL also contains histidine (1.05 mg), L-histidine hydrochloride monohydrate (4.87 mg), polysorbate 80 (0.30 mg), proline (28.78 mg), and water for injection, USP.

12 CLINICAL PHARMACOLOGY

12.1 Mechanism of Action

Rozanolixizumab-noli is a humanized IgG4 monoclonal antibody that binds to the neonatal Fc receptor (FcRn), resulting in the reduction of circulating IgG.

12.2 Pharmacodynamics

In Study 1 [see Clinical Studies (14)] , the pharmacological effect of rozanolixizumab-noli was assessed by measuring the decrease in serum IgG levels and AChR and MuSK autoantibody levels. In patients testing positive for AChR and MuSK autoantibodies who were treated with RYSTIGGO, there was a reduction in total IgG levels relative to baseline. Decreases in AChR autoantibody and MuSK autoantibody levels followed a similar pattern.

12.3 Pharmacokinetics

Rozanolixizumab-noli exhibited nonlinear pharmacokinetics. Rozanolixizumab-noli exposure increased in a greater than dose-proportional manner over a dose range from 1 mg/kg to 20 mg/kg (two times the maximum recommended dose) following subcutaneous administration.

Absorption

Following subcutaneous administration of rozanolixizumab-noli, peak plasma levels were achieved after approximately 2 days in healthy subjects.

Distribution

The apparent volume of distribution of rozanolixizumab-noli is 6.6 L.

Elimination

Metabolism

Rozanolixizumab-noli is expected to be degraded by proteolytic enzymes into small peptides and amino acids.

Excretion

The apparent clearance for the rozanolixizumab-noli is 0.89 L/day.

Specific Populations

Age, Sex, and Race

The pharmacokinetics of rozanolixizumab-noli were not affected by age, sex, or race based on a population pharmacokinetics analysis.

Patients with Renal Impairment

No dedicated pharmacokinetic study has been conducted in patients with renal impairment. Renal impairment is not expected to affect the pharmacokinetics of rozanolixizumab-noli. Based on a population pharmacokinetic analysis, which included participants with mild to moderate renal impairment, renal function (estimated glomerular filtration rate [eGFR] 38–161 mL/min/1.73 m^2) had no clinically significant effect on rozanolixizumab-noli apparent clearance. No dose adjustment is required in patients with renal impairment.

Patients with Hepatic Impairment

No dedicated pharmacokinetic study has been conducted in patients with hepatic impairment. Hepatic impairment is not expected to affect the pharmacokinetics of rozanolixizumab-noli.

Drug Interaction Studies

Clinical drug interaction studies have not been performed with rozanolixizumab-noli.

P450 Enzymes

Rozanolixizumab-noli is not metabolized by cytochrome P450 enzymes. Interactions with concomitant medications that are substrates, inducers, or inhibitors of cytochrome P450 enzymes are unlikely.

Drug Interactions with Other Drugs or Biological Products

Rozanolixizumab-noli may decrease concentrations of compounds that bind to the human FcRn [see Drug Interactions (7.1)] .

12.6 Immunogenicity

The observed incidence of anti-drug antibodies is highly dependent on the sensitivity and specificity of the assay. Differences in assay methods preclude meaningful comparisons of the incidence of anti-drug antibodies in the studies described below with the incidence of anti-drug antibodies in other studies, including those of rozanolixizumab-noli or of other rozanolixizumab products.

The anti-drug antibody (ADA) incidence from Study 1 (MG0003) was 37% (49/133) at the end of the observation period after one treatment cycle of 6-week dosing. The incidence of neutralizing antibodies was 21% (28/133). For patients who developed ADA, there was up to 60% decrease in trough concentrations compared with those in ADA negative patients. However, these observations need to be interpreted with caution because of the limitations with PK analytical assay sensitivity. There appears to be no clinically meaningful impact of ADA (including neutralizing antibodies) on efficacy of rozanolixizumab-noli. The safety profile appears to be similar in ADA positive and ADA negative patients.

13 NONCLINICAL TOXICOLOGY

13.1 Carcinogenesis, Mutagenesis, Impairment of Fertility

Carcinogenesis and Mutagenesis

Studies to assess the carcinogenic potential of rozanolixizumab-noli have not been conducted.

Studies to assess the genotoxic potential of rozanolixizumab-noli have not been conducted.

Impairment of Fertility

Subcutaneous administration of rozanolixizumab-noli (0 or 150 mg/kg) every 3 days for 26 weeks to sexually mature cynomolgus monkeys resulted in no adverse effects on sperm parameters (count, motility, or morphology) or estrus cyclicity. The dose tested in monkeys is 30 times the maximum recommended human dose of approximately 10 mg/kg, on a mg/kg/week basis.

14 CLINICAL STUDIES

The efficacy of RYSTIGGO for the treatment of generalized myasthenia gravis (gMG) in adults who are anti-AChR antibody positive or anti-MuSK antibody positive was established in a multicenter, randomized, double-blind, placebo-controlled study (Study 1; NCT03971422). The study included a 4-week screening period and a 6-week treatment period followed by 8 weeks of observation. During the treatment period, RYSTIGGO or placebo were administered subcutaneously once a week for six weeks.

Study 1 enrolled patients who met the following criteria:

- Presence of autoantibodies against AChR or MuSK
- Myasthenia Gravis Foundation of America (MGFA) Clinical Classification Class II to IVa
- Myasthenia Gravis-Activities of Daily Living (MG-ADL) total score of at least 3 (with at least 3 points from non-ocular symptoms)
- On stable dose of MG therapy prior to screening that included acetylcholinesterase (AChE) inhibitors, steroids, or non-steroidal immunosuppressive therapies (NSISTs), either in combination or alone
- Serum IgG levels of at least 5.5 g/L

In Study 1, a total of 200 patients were randomized 1:1:1 to receive weight-tiered doses of RYSTIGGO (n=133), equivalent to ≈7 mg/kg (n=66) or ≈10 mg/kg (n=67), or placebo (n=67). Baseline characteristics were similar between treatment groups. Patients had a median age of 52 years at baseline (range: 18 to 89 years) and a median time since diagnosis of 6 years. Sixty-one percent of patients were female, 68% were White, 11% were Asian, 3% were Black or African American, 1% were American Indian or Alaska Native, and 7% were of Hispanic or Latino ethnicity. Median MG-ADL total score was 8, and the median Quantitative Myasthenia Gravis (QMG) total score was 15. The majority of patients, 89.5% (n=179) were positive for AChR antibodies and 10.5% (n=21) were positive for MuSK antibodies.

At baseline in each group, over 83% of patients received AChE inhibitors, over 56% of patients received steroids, and approximately 50% received NSISTs, at stable doses.

Patients were treated with RYSTIGGO via subcutaneous infusion once per week for a period of 6 weeks [see Dosage and Administration (2.2)] , followed by an observation period of up to 8 weeks.

The efficacy of RYSTIGGO was measured using the MG-ADL scale, which assesses the impact of gMG on daily functions of 8 signs or symptoms that are typically affected in gMG. Each item is assessed on a 4-point scale where a score of 0 represents normal function and a score of 3 represents loss of ability to perform that function. A total score ranges from 0 to 24, with the higher scores indicating more impairment.

The primary efficacy endpoint was the comparison of the change from baseline between treatment groups in the MG-ADL total score at day 43. A statistically significant difference favoring RYSTIGGO was observed in the MG-ADL total score change from baseline [-3.4 points in RYSTIGGO-treated group at either dose vs -0.8 points in the placebo-treated group (p<0.001)].

The secondary endpoint was the change between treatment groups from baseline to day 43 in the QMG. The QMG is a 13-item categorical grading system that assesses muscle weakness. Each item is assessed on a 4-point scale where a score of 0 represents no weakness and a score of 3 represents severe weakness. A total possible score ranges from 0 to 39, where higher scores indicate more severe impairment.

A statistically significant difference favoring RYSTIGGO was observed in the QMG total score change from baseline [-5.4 points and -6.7 points in RYSTIGGO-treated group at ≈7 mg/kg and ≈10 mg/kg dose level, respectively, vs -1.9 points in the placebo-treated group (p<0.001)].

The results are presented in Table 3.

Table 3. Change from Baseline to Day 43 in MG-ADL and QMG Total Score in Adult Patients who are Anti-AChR or Anti-MuSK Antibody Positive (Study 1)
Efficacy Endpoints | RYSTIGGO ≈7mg/kg N = 66 | RYSTIGGO ≈10mg/kg N = 67 | Placebo N = 67
MG-ADL Total Score
LS Mean (SE) | -3.4 (0.5) | -3.4 (0.5) | -0.8 (0.5)
Difference from placebo (95% CI) | -2.6 (-4.1, -1.2) | -2.6 (-4.0, -1.2) | -
p-value | <0.001 | <0.001 | -
QMG Total Score
LS Mean (SE) | -5.4 (0.7) | -6.7 (0.7) | -1.9 (0.7)
Difference from placebo (95% CI) | -3.5 (-5.6, -1.6) | -4.8 (-6.8, -2.9) | -
p-value | <0.001 | <0.001 | -
Abbreviations: CI = confidence interval; MG-ADL, myasthenia gravis activities of daily living scale; QMG, quantitative myasthenia gravis; LS = least square; SE = standard error.

Figure 1 shows the mean change from baseline in MG-ADL score at Day 43 in Study 1.

Figure 1: Observed Mean Change from Baseline to Day 43 in MG-ADL Score

CfB=Change from Baseline; FV=Final Visit; MG−ADL=Myasthenia Gravis Activities of Daily Living.
NOTE: Error bars represent +/− standard error; arrows indicate timepoints at which treatment was given.

16 HOW SUPPLIED/STORAGE AND HANDLING

16.1 How Supplied

RYSTIGGO (rozanolixizumab-noli) injection is a sterile, preservative-free, clear to slightly opalescent, colorless to pale brownish yellow solution supplied as:

NDC | Description | Strength
50474-980-79 | 2 mL single-dose glass vial in a carton | 280 mg/2 mL
50474-981-83 | 3 mL single-dose glass vial in a carton | 420 mg/3 mL
50474-982-84 | 4 mL single-dose glass vial in a carton | 560 mg/4 mL
50474-983-86 | 6 mL single-dose glass vial in a carton | 840 mg/6 mL

16.2 Storage and Handling

Store vials refrigerated at 36°F to 46°F (2°C to 8°C) in the original carton to protect from light until the time of use. Do not freeze. Do not shake.

If needed, vials may be stored at room temperature up to 77°F (25°C) for a single period of up to 20 days in the original carton to protect the vial from light. Once a vial has been stored at room temperature, it should not be returned to the refrigerator. The discard date is 20 days after removal of the vial from the refrigerator. Write the discard date in the space provided on the carton. Discard the vial if not used within 20 days or if the expiration date has passed, whichever occurs first.

17 PATIENT COUNSELING INFORMATION

Infections

Instruct patients to communicate any history of infections to the healthcare provider and to contact their healthcare provider if they develop any symptoms of an infection [see Warnings and Precautions (5.1)] .

Vaccinations

Advise patients to complete age-appropriate vaccines according to immunization guidelines prior to initiation of a new treatment cycle with RYSTIGGO. Administration of live or live-attenuated vaccines is not recommended during treatment with RYSTIGGO [see Warnings and Precautions (5.1)] .

Aseptic Meningitis

Inform patients that RYSTIGGO could cause aseptic meningitis. Instruct patients to contact their healthcare provider if symptoms consistent with meningitis develop [see Warnings and Precautions (5.2)] .

Hypersensitivity Reactions

Inform patients about the signs and symptoms of hypersensitivity reactions. Advise patients to contact their healthcare provider immediately for signs or symptoms of hypersensitivity reactions [see Warnings and Precautions (5.3)] .

Pregnancy Registry

Advise patients that there is a registry that monitors outcomes in patients with Myasthenia Gravis, including women exposed to RYSTIGGO during pregnancy and/or breastfeeding [see Use in Specific Populations (8.1)].

Manufactured by:
UCB, Inc.
1950 Lake Park Drive
Smyrna, GA 30080

US License Number 1736

RYSTIGGO®is a registered trademark of the UCB Group of Companies.
©2025 UCB, Inc., Smyrna, GA 30080. All rights reserved.

PRINCIPAL DISPLAY PANEL - 2 mL Vial Carton

NDC 50474-980-79
Rx only

RYSTIGGO®
(rozanolixizumab-noli)
Injection

280 mg/2 mL
(140 mg/mL)

For Subcutaneous Use Only

One single-dose vial - Discard unused portion.

To be administered by a healthcare provider only.

Recommended Dosage: See prescribing information.

OPEN HERE

PRINCIPAL DISPLAY PANEL - 3 mL Vial Carton

NDC 50474-981-83
Rx only

RYSTIGGO®
(rozanolixizumab-noli)
Injection

420 mg/3 mL
(140 mg/mL)

For Subcutaneous Use Only

One single-dose vial - Discard unused portion.

To be administered by a healthcare provider only.

Recommended Dosage: See prescribing information.

OPEN HERE

PRINCIPAL DISPLAY PANEL - 4 mL Vial Carton

NDC 50474-982-84
Rx only

RYSTIGGO®
(rozanolixizumab-noli)
Injection

560 mg/4 mL
(140 mg/mL)

For Subcutaneous Use Only

One single-dose vial - Discard unused portion.

To be administered by a healthcare provider only.

Recommended Dosage: See prescribing information.

OPEN HERE

PRINCIPAL DISPLAY PANEL - 6 mL Vial Carton

NDC 50474-983-86
Rx only

RYSTIGGO®
(rozanolixizumab-noli)
Injection

840 mg/6 mL
(140 mg/mL)

For Subcutaneous Use Only

One single-dose vial - Discard unused portion.

To be administered by a healthcare provider only.

Recommended Dosage: See prescribing information.

OPEN HERE